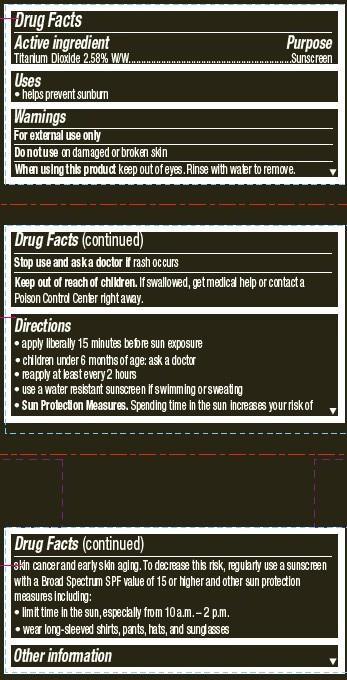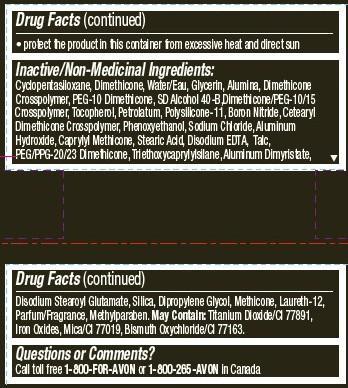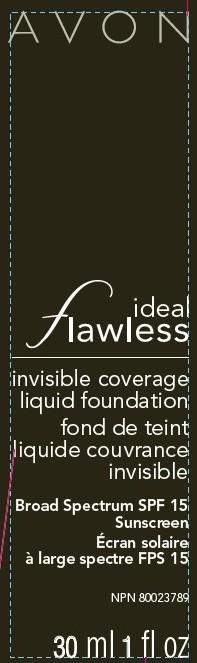 DRUG LABEL: Ideal Flawless
NDC: 10096-0257 | Form: LOTION
Manufacturer: Avon Products, Inc
Category: otc | Type: HUMAN OTC DRUG LABEL
Date: 20130207

ACTIVE INGREDIENTS: TITANIUM DIOXIDE 25.8 mg/1 mL

Active ingredient
Titanium Dioxide 2.58% W/W................................

Purpose
.................................Sunscreen

Uses
• helps prevent sunburn

Warnings
For external use only

Do not use on damaged or broken skin

When using this product keep out of eyes. Rinse with water to remove.

Stop use and ask a doctor if rash occurs

Keep out of reach of children. If swallowed, get medical help or contact a Poison Control Center right away.

Directions
• apply liberally 15 minutes before sun exposure
• children under 6 months of age: ask a doctor
• reapply at least every 2 hours
• use a water resistant sunscreen if swimming or sweating
• Sun Protection Measures. Spending time in the sun increases your risk of skin cancer and early skin aging. To decrease this risk, regularly use a sunscreen with a Broad Spectrum SPF value of 15 or higher and other sun protection measures including:
• limit time in the sun, especially from 10 a.m. – 2 p.m.
• wear long-sleeved shirts, pants, hats, and sunglasses

Other information

• protect the product in this container from excessive heat and direct sun

Inactive/Non-Medicinal Ingredients:
Cyclopentasiloxane, Dimethicone, Water/Eau, Glycerin, Alumina, Dimethicone Crosspolymer, PEG-10 Dimethicone, SD Alcohol 40-B, Dimethicone/PEG-10/15 Crosspolymer, Tocopherol, Petrolatum, Polysilicone-11, Boron Nitride, Cetearyl Dimethicone Crosspolymer, Phenoxyethanol, Sodium Chloride, Aluminum Hydroxide, Caprylyl Methicone, Stearic Acid, Disodium EDTA, Talc, PEG/PPG-20/23 Dimethicone, Triethoxycaprylylsilane, Aluminum Dimyristate, Disodium Stearoyl Glutamate, Silica, Dipropylene Glycol, Methicone, Laureth-12, Parfum/Fragrance, Methylparaben. May Contain: Titanium Dioxide/CI 77891, Iron Oxides, Mica/CI 77019, Bismuth Oxychloride/CI 77163.

Questions or Comments?
Call toll free 1-800-FOR-AVON or 1-800-265-AVON in Canada